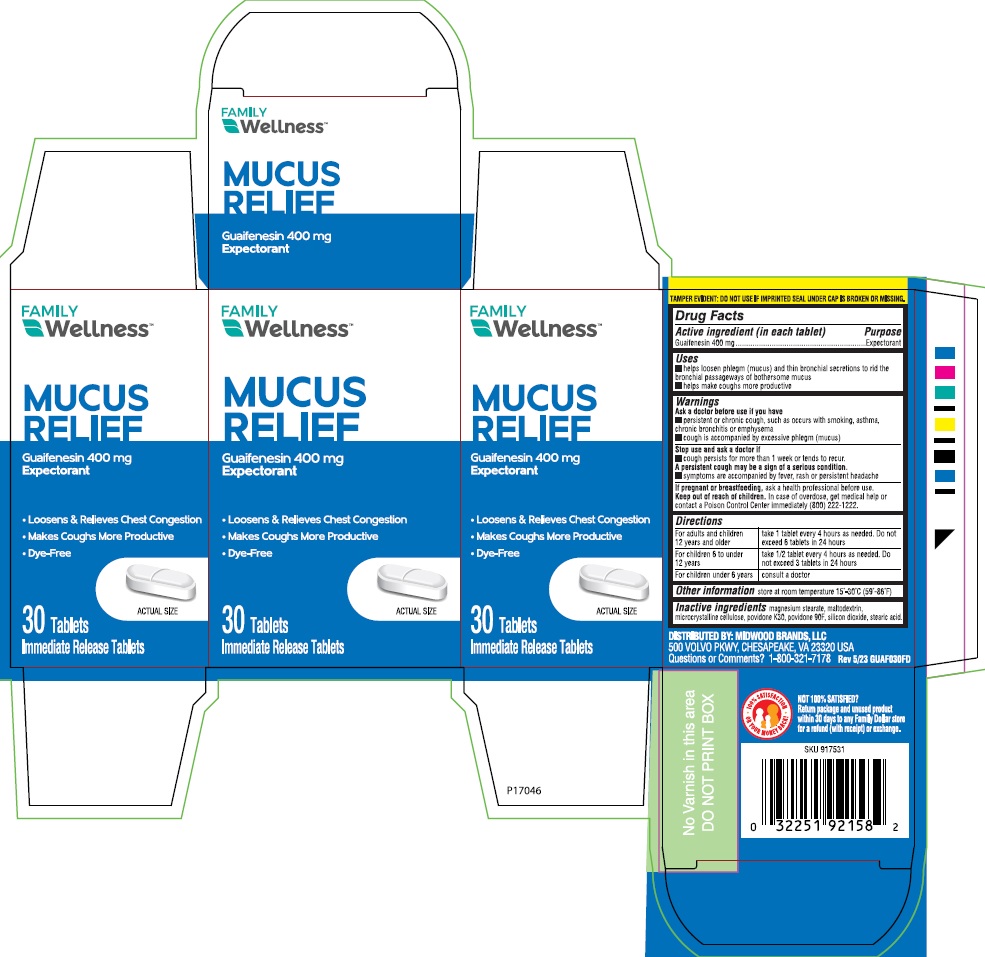 DRUG LABEL: Family Wellness Chest Congestion Relief
NDC: 55319-891 | Form: TABLET
Manufacturer: Family Dollar Services Inc
Category: otc | Type: HUMAN OTC DRUG LABEL
Date: 20241218

ACTIVE INGREDIENTS: Guaifenesin 400 mg/1 1
INACTIVE INGREDIENTS: MALTODEXTRIN; STEARIC ACID; SILICON DIOXIDE; COPOVIDONE; MAGNESIUM STEARATE; POVIDONE K90; MICROCRYSTALLINE CELLULOSE

Drug Facts

Active ingredient (per tablet)

Guaifenesin 400mg

Purpose

Expectorant

Uses

- helps loosen phlegm (mucus) and thin bronchial secretions to rid the bronchial passageways of bothersome mucus
- helps make coughs more productive

Warnings

Ask doctor before use if you have

- persistent or chronic cough, such as occurs with smoking, asthma, bronchitis or emphysema
- cough is accompanied by excessive phlegm (mucus)

Stop use and ask doctor if

- Symptoms are accompanied by fever, rash or persistent headache
- cough persists for more than 1 week or tends to recur

A persistent cough may be a sign of a serious condition.

PREGNANCY OR BREAST FEEDING

If pregnant or breast-feeding, ask a health professional before use.

Keep out of reach of children.
In case of overdose, get medical help or contact a Poison Control
Center immediately (1-800-222-1222).

Directions

- Adults and children 12 years of age and over: take 1 tablet every 4 hours as needed. Do not exceed 6 tablets in 24 hours.
- Children 6 to under 12 years of age: take 1/2 tablet every 4 hours as needed. Do not exceed 3 tablets in 24 hours.
- Children under 6 years of age: consult a doctor

Other Information

store at 15°-30°C (59°-86°F)

Inactive ingredients

magnesium stearate, microcrystalline cellulose, silicon dioxide, povidone K30, povidone 90F, maltodextrin, stearic acid.